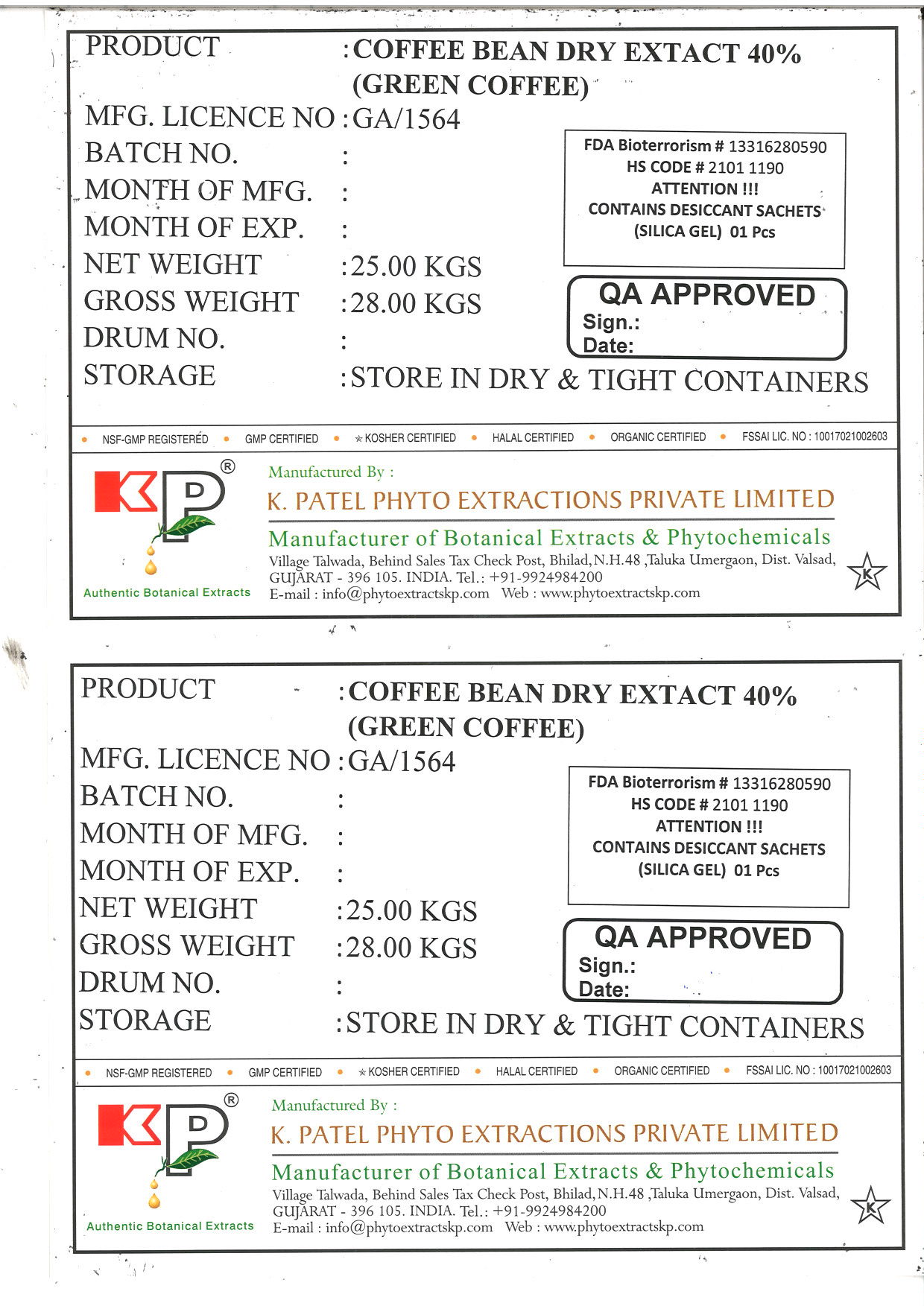 DRUG LABEL: Coffee bean dry extract 40% (Green Coffee)
NDC: 73276-008 | Form: POWDER
Manufacturer: K. Patel Phyto Extractions Private Limited
Category: other | Type: BULK INGREDIENT
Date: 20250625

ACTIVE INGREDIENTS: ARABICA COFFEE BEAN 25 kg/25 kg

Coffee ban dry extract 40% (Green coffee)